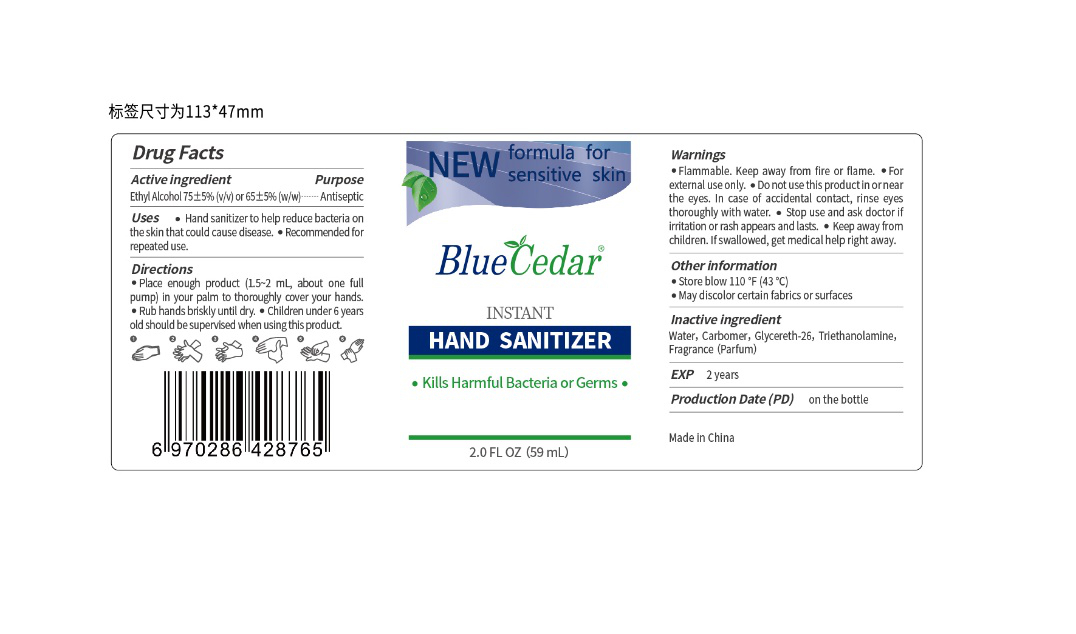 DRUG LABEL: Blue Cedar Hand Sanitizer
NDC: 55444-002 | Form: GEL
Manufacturer: Anhui Kiwi Biotech Co., Ltd.
Category: otc | Type: HUMAN OTC DRUG LABEL
Date: 20200426

ACTIVE INGREDIENTS: ALCOHOL 44.25 mL/59 mL
INACTIVE INGREDIENTS: WATER; .ALPHA.-HEXYLCINNAMALDEHYDE; .ALPHA.-TERPINEOL; TERPINEOL; .GAMMA.-NONALACTONE; LINALOOL, (+/-)-; METHYL DIHYDROJASMONATE (SYNTHETIC); CARBOMER HOMOPOLYMER, UNSPECIFIED TYPE; TROLAMINE; GLYCERETH-26; PHENYLETHYL ALCOHOL

DOSAGE AND ADMINISTRATION

Store below 110°F (43° C).
May discolor certain fabrics or surfaces.

WARNINGS

Flammable. Keep away from fire or flame.

Forexternal use only.

Do not use this product in or near the eyes. In case of accidental contact, ninse eyes thoroughly with water.

Stop use and ask doctor if iritation or rash appears andlasts.

Keep away from children. If sallowed, get medicalhelp right away,

PURPOSE

Kills Harmful Bacteria or Germs

keep out of reach of children.

INDICATIONS AND USAGE

Place enough product (1.5~-2 mL, about one full pump) in your palm to thoroughly cover your hands.

Rub hands briskly until dry.

Children under 6 years old should be supervised when using this product.

ACTIVE INGREDIENT

Ethyl Alcohol 75土 59% 6(VW) or 65士5%

INACTIVE INGREDIENT

Water, Carbomer, Glycereth :26, Triethanolamine, Fragrance (Parfum).